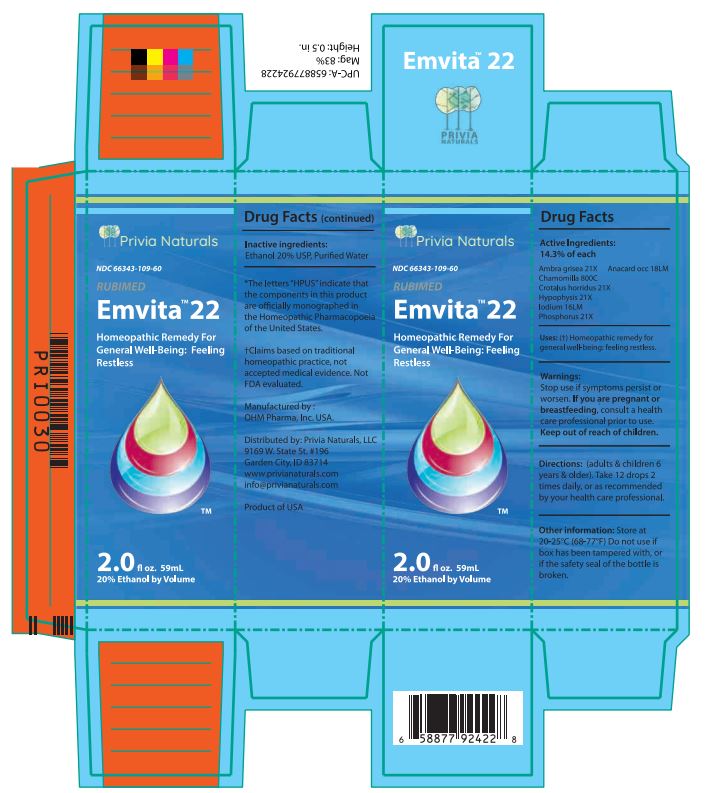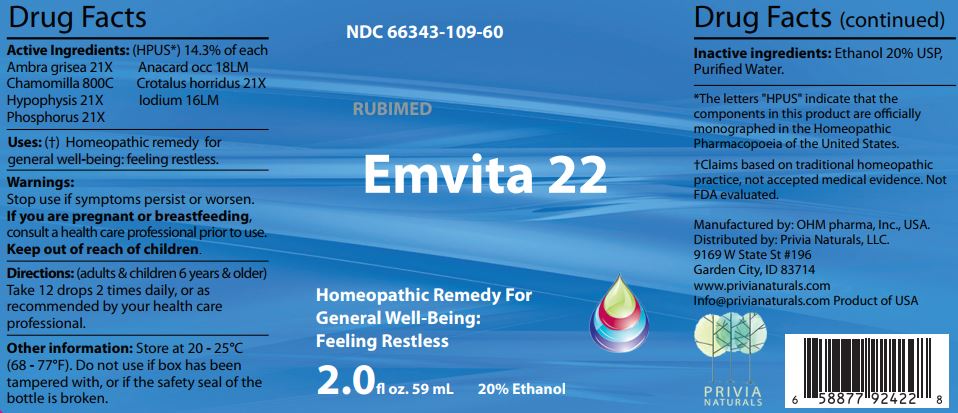 DRUG LABEL: Emvita 22
NDC: 66343-109 | Form: LIQUID
Manufacturer: RUBIMED AG
Category: homeopathic | Type: HUMAN OTC DRUG LABEL
Date: 20241129

ACTIVE INGREDIENTS: AMBERGRIS 21 [hp_X]/60 mL; ANACARDIUM OCCIDENTALE FRUIT 18 [hp_M]/60 mL; MATRICARIA CHAMOMILLA WHOLE 800 [hp_C]/60 mL; CROTALUS HORRIDUS HORRIDUS VENOM 21 [hp_X]/60 mL; SUS SCROFA PITUITARY GLAND 21 [hp_X]/60 mL; IODINE 16 [hp_M]/60 mL; PHOSPHORUS 21 [hp_X]/60 mL
INACTIVE INGREDIENTS: ALCOHOL; WATER

Emvita 22

ACTIVE INGREDIENT

Drug Facts Active Ingredients: (HPUS*) 14.3% of each

Ambra grisea 21X Anacard occ 18LM
Chamomilla 800C Crotalus horridus 21X
Hypophysis 21X Iodium 16LM
Phosphorus 21X

*The letters "HPUS" indicate that the components in this product are officially monographed in the Homeopathic Pharmacopoeia of the United States. †Claims based on traditional homeopathic practice, not accepted medical evidence. Not FDA evaluated.

INDICATIONS AND USAGE

Uses: (†) Homeopathic remedy for general well being: feeling restless.

Warnings:

Stop use if symptoms persist or worsen.

If you are pregnant or breastfeeding,consult a healthcare professional prior to use.

Keep out of reach of children.

DOSAGE AND ADMINISTRATION

Directions: (adults & children 6 years & older)

Take 12 drops 2 times daily, or as recommended by your health care professional.

Other information: Store at 20 - 25°C

(68 - 77°F.) Do not use if box has been

tampered with, or if the safety seal of the

bottle is broken.

Inactive ingredients:Ethanol 20% USP,

Purified Water.

QUESTIONS

Manufactured by: OHM pharma, Inc, USA.

Distributed by: Privia Naturals, LLC.

9169 W State St #196

Garden City, ID 83714

www.privianaturals.com

Info@privianaturals.com Product of USA.

PACKAGE LABEL

NDC 66343-109-60

RUBIMED

Emvita 22

Homeopathic Medicine For

General Well-being:

Feeling Restless

2.0 fl oz. 59mL 20% Ethanol

PURPOSE

Homeopathic Medicine For

General Well-being:

Feeling Restless